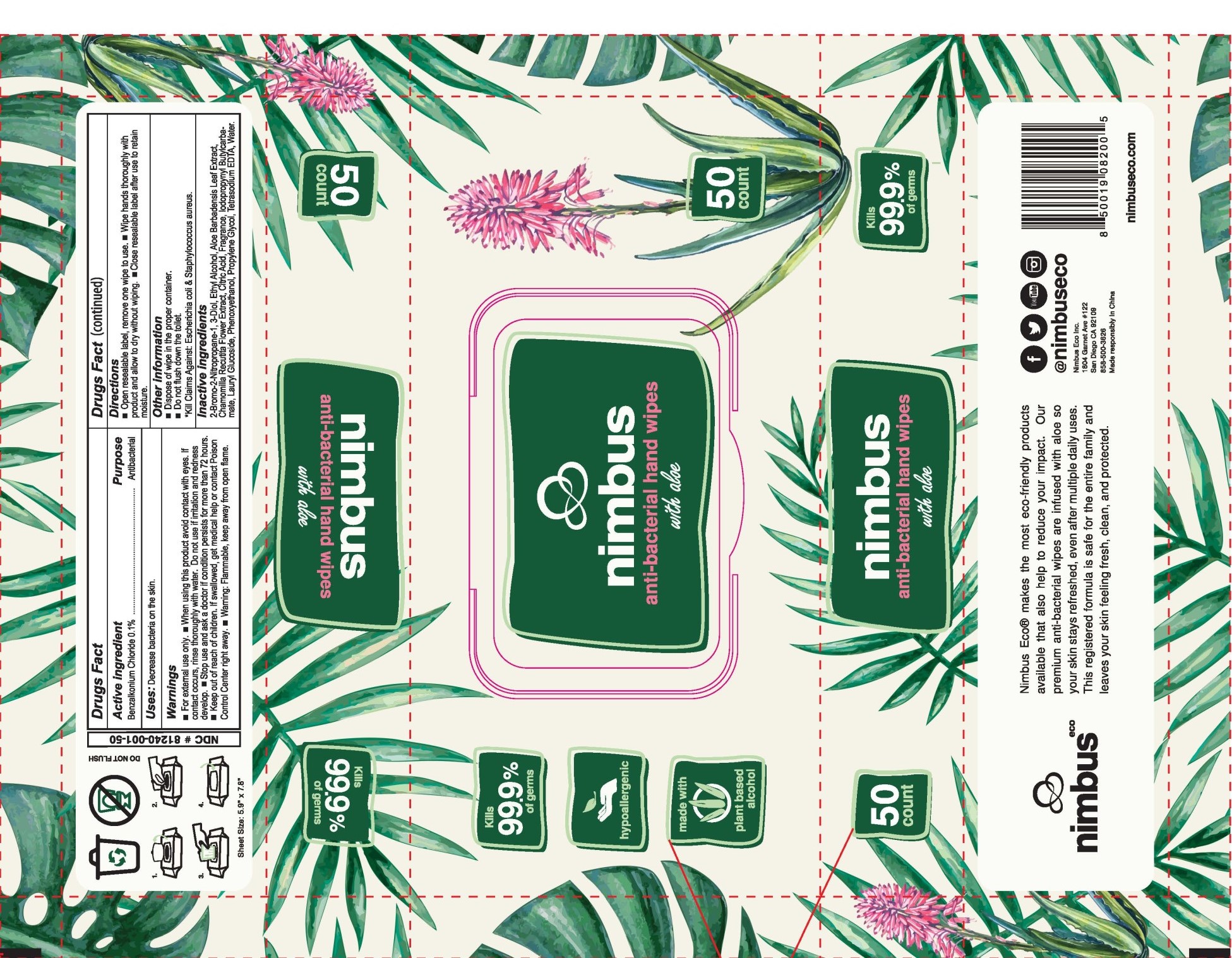 DRUG LABEL: Nimbus
NDC: 81240-001 | Form: CLOTH
Manufacturer: Nimbus Eco Inc.
Category: otc | Type: HUMAN OTC DRUG LABEL
Date: 20220113

ACTIVE INGREDIENTS: BENZALKONIUM CHLORIDE 0.12 mg/100 mL
INACTIVE INGREDIENTS: CHAMOMILE FLOWER OIL 0.01 mL/100 mL; ALCOHOL 5 mL/100 mL; ALOE VERA LEAF 0.01 mL/100 mL; BRONOPOL 0.1 mL/100 mL; LAURYL GLUCOSIDE 0.5 mL/100 mL; PHENOXYETHANOL 0.5 mL/100 mL; WATER 88.36 mL/100 mL; PROPYLENE GLYCOL 5 mL/100 mL; IODOPROPYNYL BUTYLCARBAMATE 0.1 mL/100 mL; CITRIC ACID MONOHYDRATE 0.1 mL/100 mL; EDETATE SODIUM 0.1 mL/100 mL; CHAMOMILE 0.1 mL/100 mL

This is a hand sanitizing wipe manufactured using only the following United States Pharmacopoeia (USP) grade ingredients

1. Benzalkonium Chloride (USP grade) (0.12%, volume/volume (v/v))
2. Water
  c. Propylene Glycol
  d. Ethyl Alcohol
  e. Lauryl Glucoside
  f. Phenoxyethanol
  g. Tetrasodium EDTA
  h. 3-Iodo-2-Propynyl ButylCarbamate
  i. 2-Bromo-2-Nitropropane-1,3-Diol
  j. Citric Acid
  k. Fragrance
  l. Aloe Barbadensis Leaf Extract
  m. Chamomilla Recutita Flower Extract

Active Ingredient(s)

Benzalkonium Chloride 0.1% Purpose: Antibacterial

Purpose

Antibacterial

Use

Decrease bacteria on the skin

Warnings

For external use only.

Do not use if irritation and redness develop

When using this product avoid contact with eyes, if contact occurs, rinse thoroughly with water.

Stop use and ask a doctor if condition persists for more than 72 hours.

Keep out of reach of children. If swallowed, get medical help or contact a Poison Control Center right away.

Directions

Open resealable label. Remove one wipe to use. Wipe hands thoroughly with product and allow to dry without wiping.

Close resealable label after use to retain moisture.

Other information

Dispose of wipe in the proper container

Do not flush down the toilet

Kill claims against: Escherichia Coli and Staphylococcus aureus

Inactive ingredients

Water
Propylene Glycol
Ethyl Alcohol
Lauryl Glucoside
Phenoxyethanol
Benzalkonium Chloride
Tetrasodium EDTA
3-Iodo-2-Propynyl ButylCarbamate
2-Bromo-2-Nitropropane-1,3-Diol
Citric Acid
Fragrance N/A
Aloe Barbadensis Leaf Extract
Chamomilla Recutita Flower Extract

Package Label - Principal Display Panel

50 count NDC: 81240-001-50